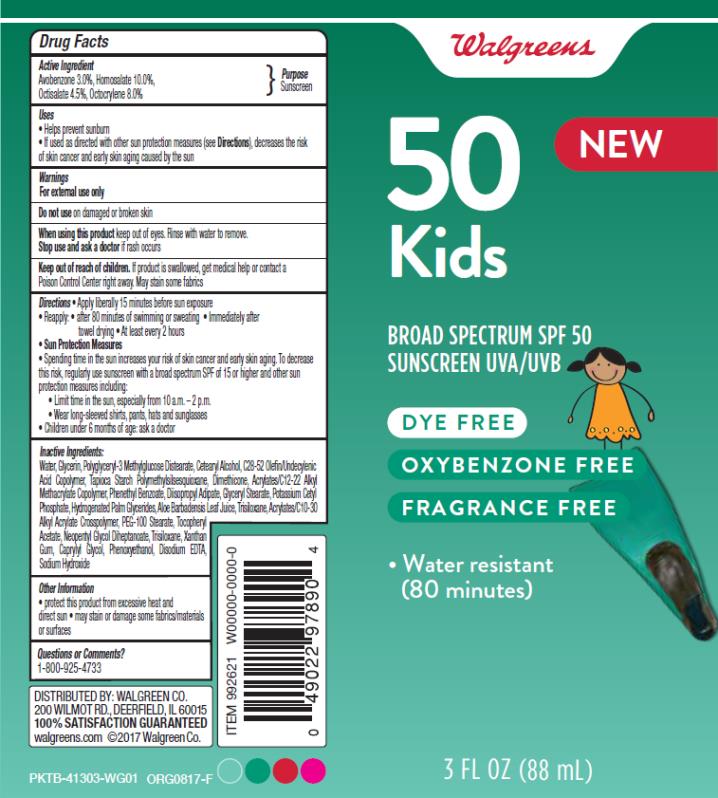 DRUG LABEL: Walgreens Sun Kids SPF50
NDC: 0363-9921 | Form: LOTION
Manufacturer: Walgreen Company
Category: otc | Type: HUMAN OTC DRUG LABEL
Date: 20171005

ACTIVE INGREDIENTS: AVOBENZONE 3 g/100 g; HOMOSALATE 10 g/100 g; OCTISALATE 4.5 g/100 g; OCTOCRYLENE 8 g/100 g
INACTIVE INGREDIENTS: CARBOMER INTERPOLYMER TYPE A (55000 CPS); ALOE VERA LEAF; CAPRYLYL GLYCOL; CETOSTEARYL ALCOHOL; DIISOPROPYL ADIPATE; DIMETHICONE; EDETATE DISODIUM ANHYDROUS; GLYCERIN; GLYCERYL MONOSTEARATE; HYDROGENATED PALM GLYCERIDES; NEOPENTYL GLYCOL DIHEPTANOATE; POLYOXYL 100 STEARATE; PHENETHYL BENZOATE; PHENOXYETHANOL; POTASSIUM CETYL PHOSPHATE; SODIUM HYDROXIDE; ALPHA-TOCOPHEROL ACETATE; TRISILOXANE; WATER; XANTHAN GUM

WAG sun Kids lot SPF50 tube 3oz

1491-25 Rev 00

Walgreens Kids Sunscreen Lotion

Active Ingredients

Avobenzone 3%, Homosalate 10%, Octocrylene 8%, Octisalate 4.5%

Purpose

Sunscreen

Uses

- helps prevent sunburn
- if used as directed with other sun protection measures (see Directions), decreases the risk of skin cancer and early skin aging caused by the sun

Warnings

For external use only

Do not use

on damaged or broken skin

When using this product

keep out of eyes. Rinse with water to remove.

Stop use and ask a doctor

if rash occurs

Keep out of reach of children.

If swallowed, get medical help or contact a Poison Control Center right away.

Directions

- apply liberally 15 minutes before sun exposure
- reapply:
  • after 80 minutes of swimming or sweating
  • immediately after towel drying
  • at least every 2 hours
- Sun Protection Measures. Spending time in the sun increases your risk of skin cancer and early skin aging. To decrease this risk, regularly use a sunscreen with a Broad Spectrum SPF of 15 or higher and other sun protection measures including:
  • limit time in the sun, especially from 10 a.m. - 2 p.m.
  • wear long-sleeve shirts, pants, hats, and sunglasses
- children under 6 months: Ask a doctor

Inactive Ingredients

Acrylates/C10-30 Alkyl Acrylate Crosspolymer, Acrylates/C12-22 Alkyl Methacrylate Copolymer, Aloe Barbadensis Leaf Juice, C28-52 Olefin/Undecylenic Acid , Caprylyl Glycol, Cetearyl Alcohol, Diisopropyl Adipate, Dimethicone, Disodium EDTA, Fragrance, Glycerin, Glyceryl Stearate, Hydrogenated Palm Glycerides, Neopentyl Glycol Diheptanoate, PEG 100 Stearate, Phenethyl Benzoate, Polyglyceryl-3 Methylglucose Distearate, Phenoxyethanol, Potassium Cetyl Phosphate, Sodium Hydroxide, Tapioca Starch Polymethylsilsesquioxane, Tocopherol Acetate, Trisiloxane, Water, Xanthan Gum

Other Information

- for use on skin only. Avoid contact with fabric
- protect this product from excessive heat and direct sun

Questions or comments?

www.walgreens.com or call toll free 1-800-XXX-XXXX

PRINCIPAL DISPLAY PANEL

50
Kids
Broad Spectrum SPF 50
Sunscreen UVA/UVB
Dye Free
Oxybenzone Free
3 FL OZ (88 mL)